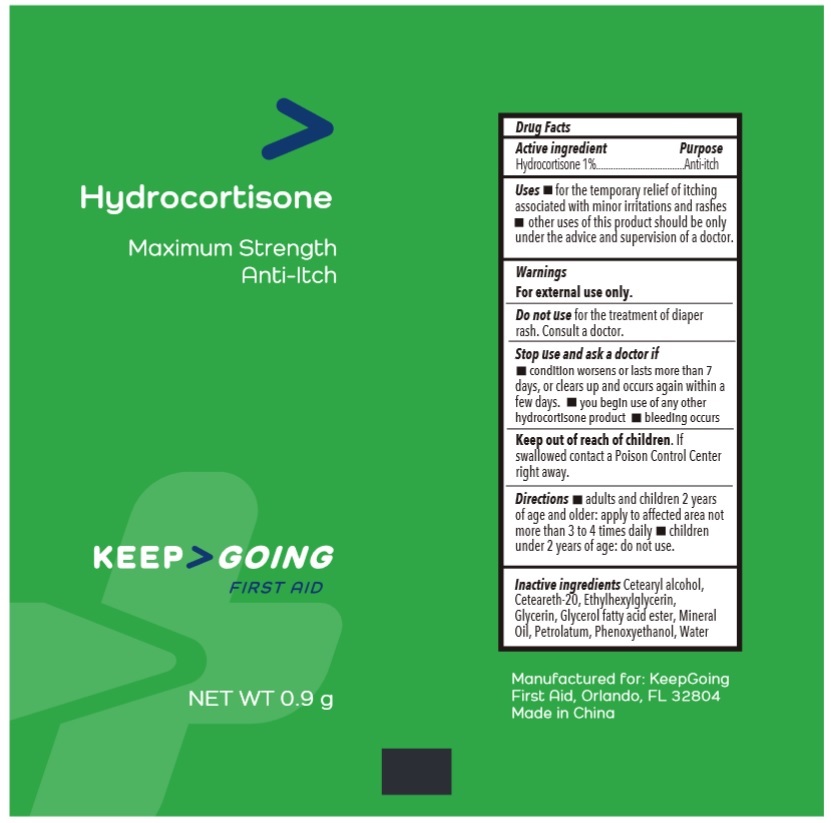 DRUG LABEL: Hydrocortisone
NDC: 82942-1003 | Form: CREAM
Manufacturer: J&A Digital Inc.
Category: otc | Type: HUMAN OTC DRUG LABEL
Date: 20241210

ACTIVE INGREDIENTS: HYDROCORTISONE 10 mg/1 g
INACTIVE INGREDIENTS: CETOSTEARYL ALCOHOL; POLYOXYL 20 CETOSTEARYL ETHER; ETHYLHEXYLGLYCERIN; GLYCERIN; MINERAL OIL; PETROLATUM; PHENOXYETHANOL; WATER

Hydrocortisone

Active ingredient

Hydrocortisone 1%

Purpose

Anti-itch

Uses

- for the temporary relief of itching associated with minor irritations and rashes
- other uses of this product should be only under the advice and superivision of a doctor.

Warnings

For external use only.

Do not use

for the treatment of diaper rash. Consult a doctor.

Stop use and ask a doctor if

- condition worsens of lasts more than 7 days, or clears up and occurs again within a few days.
- you begin use of any other hydrocortisone product
- bleeding occurs

Keep out of reach of children.

If swallowed contact a Poison Control Center right away.

Directions

- adults and children 2 years of age and older: apply to affected area not more than 3 to 4 times daily
- children under 2 years of age: do not use.

Inactive ingredients

Cetearyl alcohol, Ceteareth-20, Ethylhexylglycerin, Glycerin, Glycerol fatty acid ester, Mineral Oil, Petrolatum, Phenoxyethanol, Water